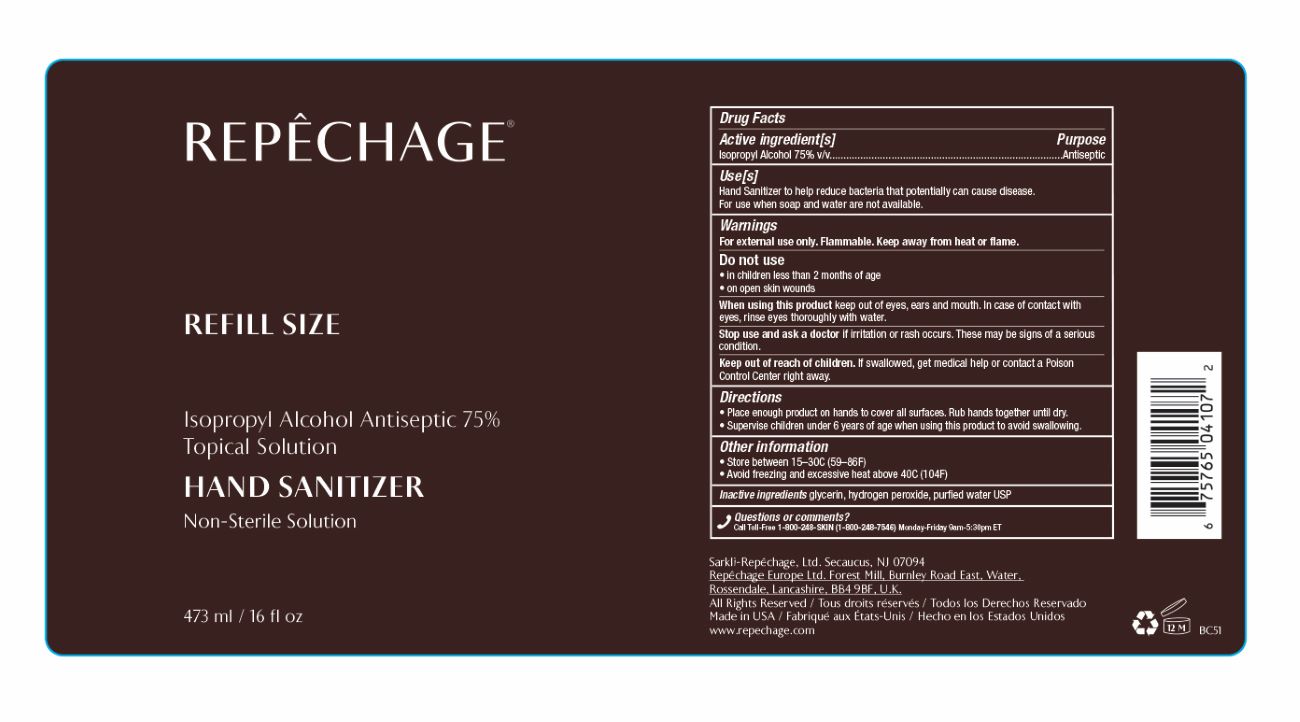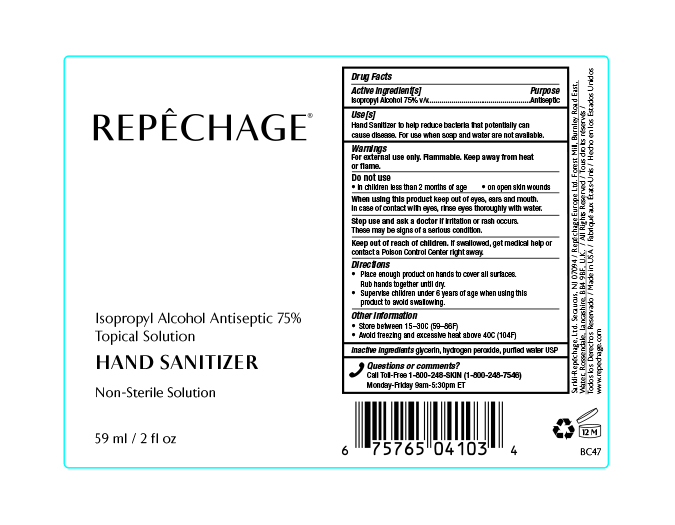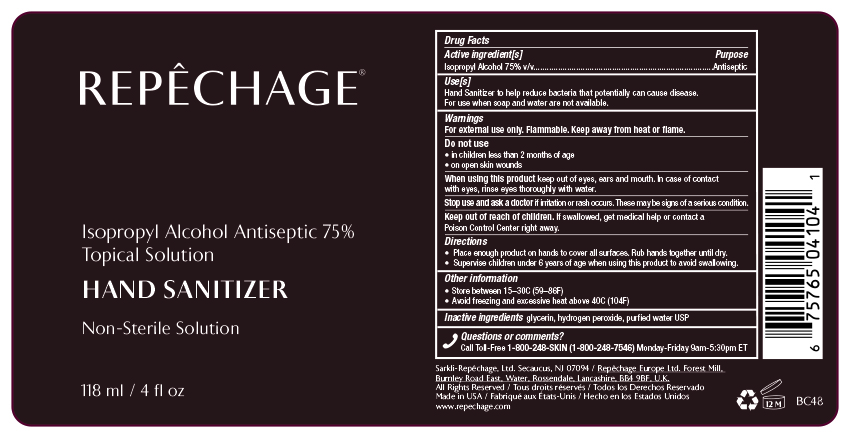 DRUG LABEL: Isopropyl Alcohol Antiseptic 75% Topical Solution Hand Sanitizer Non-Sterile Solution
NDC: 64521-1234 | Form: SOLUTION
Manufacturer: Sarkli-Repechage, Ltd.
Category: otc | Type: HUMAN OTC DRUG LABEL
Date: 20200427

ACTIVE INGREDIENTS: ISOPROPYL ALCOHOL 75 mL/100 mL
INACTIVE INGREDIENTS: GLYCERIN; HYDROGEN PEROXIDE; WATER

Repechage Isopropyl Alcohol Antiseptic 75% Topical Solution Hand Sanitizer Non-Sterile Solution

Drug Facts
Active ingredient[s] Purpose
Isopropyl alcohol 75% v/v..........................................................................Antiseptic

Purpose
Antiseptic

INDICATIONS AND USAGE

Use[s]
Hand Sanitizer to help reduce bacteria that potentially can cause disease.
For use when soap and water are not available.

Warnings
For external use only. Flammable. Keep away from heat or flame.

Do not use
• in children less than 2 months of age
• on open skin wounds

When using this product keep out of eyes, ears and mouth. In case of contact
with eyes, rinse eyes thoroughly with water.

STOP USE

Stop and ask a doctor if irritation or rash occurs. These may be signs of a serious
condition.

Keep out of reach of children. If swallowed, get medical help or contact a
Poison Control Center right away.

Directions
• Place enough product on hands to cover all surfaces. Rub hands together until dry.
• Supervise children under 6 years of age when using this product to avoid swallowing.

Directions
• Place enough product on hands to cover all surfaces. Rub hands together until dry.
• Supervise children under 6 years of age when using this product to avoid swallowing.

Other information
• Store between 15–30C (59–86F)
• Avoid freezing and excessive heat above 40C (104F)

Inactive ingredients glycerin, hydrogen peroxide, purfied water USP

Questions or comments?
Call Toll-Free 1-800-248-SKIN (1-800-248-7546) Monday-Friday 9am-5:30pm ET

Repechage Isopropyl Alcohol Antiseptic 75% Topical Solution Hand Sanitizer Non-Sterile Solution

118 mL NDC 64521-1234-4

59 mL NDC 64521-1234-2

473 mL NDC 64521-1234-1